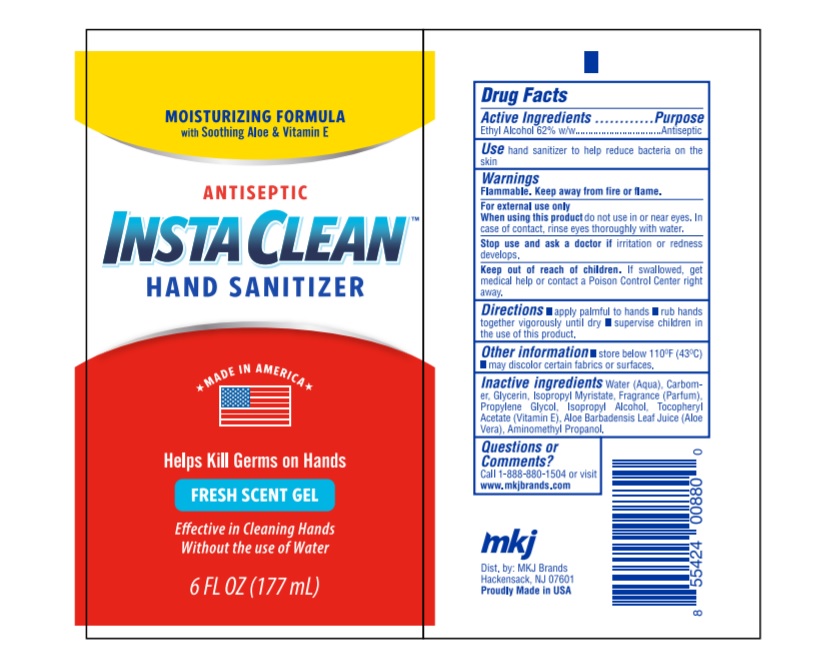 DRUG LABEL: Insta Clean
NDC: 57768-001 | Form: GEL
Manufacturer: Omega Packaging Corporation
Category: otc | Type: HUMAN OTC DRUG LABEL
Date: 20200513

ACTIVE INGREDIENTS: ALCOHOL 62 mL/100 mL
INACTIVE INGREDIENTS: CARBOMER COPOLYMER TYPE A; GLYCERIN; PROPYLENE GLYCOL; .ALPHA.-TOCOPHEROL ACETATE; AMINOMETHYLPROPANOL; ISOPROPYL MYRISTATE; ALOE; TROLAMINE; WATER

Insta Clean Hand Sanitizer

Active Ingredient

Ethyl alcohol 62%. w/w......................Antiseptic

Purpose

Antiseptic

INDICATIONS AND USAGE

For handwashing to decrease bacteria on the skin.

Warnings

Flammable, keep away from fire or flame. For external use only.

When using this produc

Avoid contact with eyes. In case of contact flush eyes with water.

Stop use and ask a doctor

If redness or irritation develop and persist for more than 72 hours.

Keep out of reach of children

If swallowed get medical help or contact a Poison Control Center right away.

Directions

apply palmful to hand , rub hand together vigorously until dry , supervise children in the use of this product.

other information

store below 110 °F,(43.33 °C) may discolor certain fabrics or surfaces.

INACTIVE INGREDIENT

Inactive Ingredients: Water, Isopropyl Alcohol, Glycerin, Carbomer, Aminomethyl Propanol, Fragrance, Propylene Glycol, Isopropyl Myristate, Aloe Barbadensis Leaf Juice (Aloe Vera) Tocopheryl Acetate (Vitamin E)